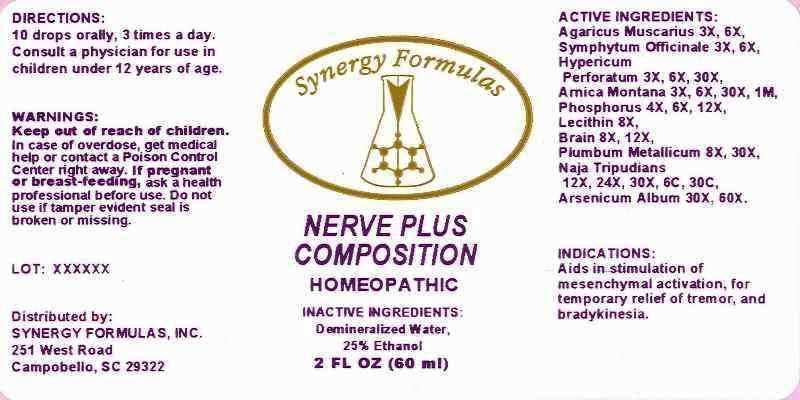 DRUG LABEL: Nerve Plus Composition
NDC: 43772-0030 | Form: LIQUID
Manufacturer: Synergy Formulas, Inc.
Category: homeopathic | Type: HUMAN OTC DRUG LABEL
Date: 20140311

ACTIVE INGREDIENTS: AMANITA MUSCARIA FRUITING BODY 3 [hp_X]/1 mL; COMFREY ROOT 3 [hp_X]/1 mL; HYPERICUM PERFORATUM 3 [hp_X]/1 mL; ARNICA MONTANA 3 [hp_X]/1 mL; PHOSPHORUS 4 [hp_X]/1 mL; EGG PHOSPHOLIPIDS 8 [hp_X]/1 mL; PORK BRAIN 8 [hp_X]/1 mL; LEAD 8 [hp_X]/1 mL; NAJA NAJA VENOM 12 [hp_X]/1 mL; ARSENIC TRIOXIDE 30 [hp_X]/1 mL
INACTIVE INGREDIENTS: WATER; ALCOHOL

Drug Facts

ACTIVE INGREDIENTS:

Agaricus Muscarius 3X, 6X, Symphytum Officinale 3X, 6X, Hypericum Perforatum 3X, 6X, 30X, Arnica Montana 3X, 6X, 30X, 1M, Phosphorus 4X, 6X, 12X, Lecithin 8X, Brain 8X, 12X, Plumbum Metallicum 8X, 30X, Naja Tripudians 12X, 24X, 30X, 6C, 30C, Arsenicum Album 30X, 60X.

INDICATIONS:

Aids in stimulation of mesenchymal activation, for temporary releif of tremor, and bradykinesia.

WARNINGS:

Keep out of reach of children. In case of overdose, get medical help or contact a Posion Control Center right away. If pregnant or breast-feeding, ask a health professional before use. Do not use if tamper evident seal is broken or missing.

DIRECTIONS:

10 drops orally, 3 times a day. Consult a physician for use in chiildren under 12 years of age.

INACTIVE INGREDIENTS:

Demineralized Water, 25% Ethanol

Keep out of reach of children. In case of overdose, get medical help or contact a Posion Control Center right away.

INDICATIONS:

Aids in stimulation of mesenchymal activation, for temporary releif of tremor, and bradykinesia.

QUESTION:

Distributed by:

SYNERGY FORMULAS, INC.

251 West Road

Campobello, SC 29322

Package Display Label

Synergy Formulas

NERVE PLUS COMPOSITION

HOMEOPATHIC

2 FL OZ (60ml)